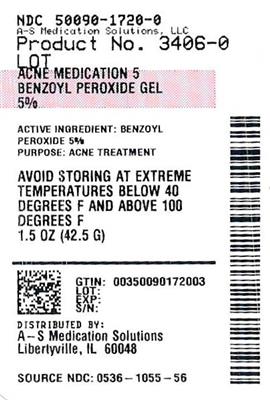 DRUG LABEL: Rugby Benzoyl Peroxide 
NDC: 50090-1720 | Form: GEL
Manufacturer: A-S Medication Solutions
Category: otc | Type: HUMAN OTC DRUG LABEL
Date: 20241106

ACTIVE INGREDIENTS: BENZOYL PEROXIDE 50 mg/1 mL
INACTIVE INGREDIENTS: CELLULOSE GUM; Edetate Disodium; Laureth-4; Sodium Hydroxide; CI 77891; Water

Rugby® 5% Benzoyl Peroxide Gel
Acne Medication

Drug Facts

Active ingredient

Benzoyl peroxide 5%

Purpose

Acne treatment

Use

for the treatment of acne

Warnings

For external use only

Do not use this medication if you have very sensitive skin or if you are sensitive to benzoyl peroxide.

When using this product

n keep away from eyes, lips and mouth

- avoid unnecessary sun exposure and use a sunscreen
- avoid contact with hair or dyed fabric, including carpet and clothing which may be bleached by this product
- skin irritation may occur, characterized by redness, burning, itching, peeling, or possibly swelling. Mild irritation may be reduced by using the product less frequently or in a lower concentration. If irritation becomes severe, discontinue use; if irritation still continues, consult a doctor.
- using other topical acne medication at the same time or immediately following the use of this product may increase dryness or irritation of the skin. If this occurs, only one medication should be used unless directed by a doctor.

Keep out of reach of children. If swallowed, get medical help or contact a Poison Control Center right away. Avoid contact with the eyes. If contact occurs, flush thoroughly with water.

Directions

Cleanse skin thoroughly before applying medication. Cover the entire affected area with a thin layer 1-3 times daily. If bothersome dryness or peeling occurs, reduce application to once a day.

Other information

Keep tightly closed. Avoid storing at extreme temperatures (below 40° F and above 100° F).

Inactive ingredients

carbomer, disodium EDTA, laureth-4, sodium hydroxide, titanium dioxide, water

Questions or comments?

1-800-645-2158

Distributed by:
Rugby Laboratories
31778 Enterprise Drive
Livonia, MI 48150

HOW SUPPLIED

Product: 50090-1720

NDC: 50090-1720-0 42.5 mL in a TUBE / 1 in a CARTON